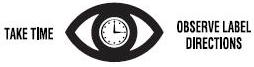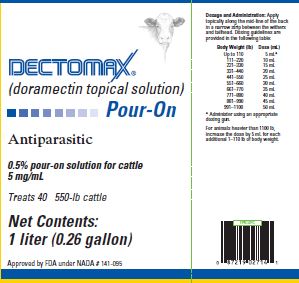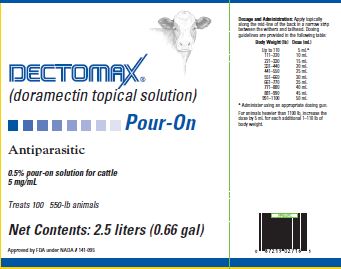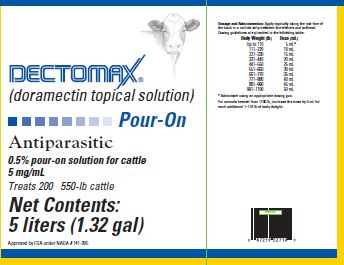 DRUG LABEL: Dectomax
NDC: 54771-2718 | Form: SOLUTION
Manufacturer: Zoetis Inc.
Category: animal | Type: OTC ANIMAL DRUG LABEL
Date: 20230724

ACTIVE INGREDIENTS: DORAMECTIN 5 mg/1 mL

DECTOMAX® Pour-On

DECTOMAX®
(doramectin topical solution)
Pour-On

Antiparasitic

0.5% pour-on solution for cattle
5 mg/mL

PRODUCT DESCRIPTION

Dectomax Pour-On solution is a ready-to-use, systemically active, clear, light blue solution containing 0.5% w/v doramectin (5 mg/mL). It is formulated to deliver the recommended dosage of 500 mcg/kg (227 mcg/lb) of body weight when given by topical administration at the rate of 1 mL/22 lb (10 kg) of body weight.

PRODUCT CHARACTERISTICS

Dectomax Pour-On solution is a highly active, broad-spectrum parasiticide for topical administration to cattle. It contains doramectin, a novel fermentation-derived macrocyclic lactone discovered by Pfizer Inc. Doramectin is isolated from fermentations of selected strains derived from the soil organism Streptomyces avermitilis.

A primary mode of action of macrocyclic lactones is to modulate chloride ion channel activity in the nervous system of nematodes and arthropods. Macrocyclic lactones bind to receptors that increase membrane permeability to chloride ions. This inhibits the electrical activity of nerve cells in nematodes and muscle cells in arthropods and causes paralysis and death of the parasites. In mammals, the neuronal receptors to which macrocyclic lactones bind are localized within the central nervous system (CNS), a site reached by only negligible concentrations of doramectin.

One dose of Dectomax Pour-On solution effectively treats and controls a wide range of roundworm and arthropod parasites that impair the health and productivity of cattle.

Studies have demonstrated the safety margin of doramectin. In USA trials, no toxic signs were seen in cattle given up to 25 times the recommended dose of Dectomax Injectable solution. A study using Dectomax Injectable solution also demonstrated safety in neonatal calves treated with up to 3 times the recommended dose. In breeding animals (bulls, and cows during folliculogenesis, organogenesis, implantation, and through gestation), a dose 3 times the recommended dose of Dectomax Injectable solution had no effect on breeding performance. A pharmacokinetic study demonstrated that systemic exposure to doramectin from Dectomax Pour-On was less than systemic exposure to doramectin from Dectomax Injectable solution.

PRODUCT INDICATIONS

Dectomax Pour-On solution is indicated for the treatment and control of the following species of gastrointestinal roundworms, lungworms, eyeworms, grubs (see PRECAUTIONS), biting and sucking lice, horn flies, and mange mites in cattle. Consult your veterinarian for assistance in the diagnosis, treatment, and control of parasitism.

Gastrointestinal roundworms
Ostertagia ostertagi (adults and L4, including inhibited larvae)
O. lyrata (adults)
Haemonchus placei (adults and L4)
Trichostrongylus axei (adults and L4)
T. colubriformis (adults and L4)
Cooperia oncophora (adults [Efficacy below 90% was observed against adult C. oncophora in some clinical studies.] and L4)
C. pectinata (adults)
C. punctata (adults and L4)
C. surnabada (adults)
Bunostomum phlebotomum (adults)
Oesophagostomum radiatum (adults and L4)
Trichuris spp. (adults)

Lungworms (adults and fourth stage larvae)
Dictyocaulus viviparus

Eyeworms | Grubs
Thelazia gulosa (adults) | Hypoderma bovis
T. skrjabini (adults) | H. lineatum
Lice | Horn Flies
Biting Lice | Haematobia irritans
Bovicola (Damalinia) bovis | Mange Mites
Sucking Lice | Chorioptes bovis
Haematopinus eurysternus | Sarcoptes scabiei
Linognathus vituli
Solenopotes capillatus

Dectomax Pour-On solution has been proved to effectively control infections and to protect cattle from reinfection with Cooperia oncophora, Dictyocaulus viviparus, Ostertagia ostertagi, and Oesophagostomum radiatum for 28 days; and Cooperia punctata and Haemonchus placei for 35 days after treatment.

Dectomax Pour-On solution has been proved to effectively control infestations and to protect cattle from reinfestation with Bovicola (Damalinia) bovis for 77 days and Linognathus vituli for 42 days after treatment.

Management Considerations for Horn Flies

Dectomax Pour-On solution provides 7 days of persistent activity against horn flies. The product should be used as part of an integrated control program and be combined with other methods for extended horn fly control. For optimal horn fly control, consult with your veterinarian or a livestock entomologist.

DOSAGE

Administer Dectomax Pour-On solution to cattle topically at a dosage of 500 mcg doramectin per kg (227 mcg/lb) of body weight. Each mL contains 5 mg of doramectin, sufficient to treat 22 lb (10 kg) of body weight.

For the best results, Dectomax Pour-On solution should be a part of a parasite control program for both internal and external parasites based on the epidemiology of these parasites. Consult a veterinarian or an entomologist for information regarding the most effective timing of applications.

Do not underdose. Ensure each animal receives a complete dose based on a current body weight. Underdosing may result in ineffective treatment, and encourage the development of parasite resistance.

ADMINISTRATION

Dectomax Pour-On solution should be applied topically along the mid-line of the back in a narrow strip between the withers and tailhead.

Dosing Cup (1-L bottles)

A dosing cup is provided for use with Dectomax Pour-On solution supplied in 1-L bottles. The Dectomax Pour-On solution dosing cup should be installed by rotating the cup on the bottle neck until tight. When installed correctly, the spout is aligned at the mid-point on the wide side of the bottle.
The curved end of the dosing cup tube should be positioned at the bottom of the bottle on the side opposite the spout. When the dosing cup is in the closed position (“zero” at set dosage mark on screw), product does not enter the cup reservoir. Select a dose [1 mL per 22 lb (10 kg) of body weight] by twisting the dosing screw on the top of the dosing cup to the desired position. The first complete turn of the dosing screw will set the dose at 10 mL (“10” shows on the screw at set dose mark). Each additional turn increases the dose in 5 mL increments until a maximum dose of 50 mL (“50” is the bottom number showing on screw at the set dose mark) is reached. When body weight is between weight markings on the dosing cup, use the higher dose volume.
To fill the dosing reservoir, hold the bottle upright and squeeze it until a slight excess has been delivered as indicated by the calibration lines. Release the pressure and excess will automatically drain from the reservoir and return to the bottle.
Tilt the bottle to deliver the dose. Dectomax Pour-On solution should be delivered to cattle on the back in a single pass from the withers to the tailhead.

Applicators (2.5-L and 5-L bottles)

Applicators are available for use with Dectomax Pour-On solution supplied in 2.5- and 5-L backpacks. Directions for 2 recommended applicators are provided below. Some applicators may be incompatible with this formulation.

Phillips Pour-on Applicator System

- Replace the shipping cap on 2.5- or 5-L backpack with the draw-off cap provided and tighten firmly.
- Thread the draw-off tubing through the anti-kink spring. Attach the tube to the draw-off cap. Screw the spring counter clockwise over the tubing and draw-off spigot.
- Invert the backpack.
- Set the dose to maximum (50 mL). Gently prime the applicator, checking for leaks. To prime, place the nozzle into a clean, dry receptacle and depress lever fully. Pump 3–4 short strokes ensuring that the piston reaches the end of the cylinder, and then release the lever completely to fill the cylinder. A small air bubble may appear within the cylinder. This will not affect the dosing accuracy.
- Set the required dose and administer.
- To disconnect the system, proceed as follows:
  - a)Set backpack in upward position.
  - b)Discharge residual material from the applicator and draw-off tubing into a separate, clean, dry receptacle.
- Follow the manufacturer's recommendation for care and maintenance of the dosing applicator.
- Remove the draw-off cap. Replace with the original cap and tighten firmly.

Syrvet Pour-on Applicator System

- Replace the shipping cap on the 2.5- or 5-L backpack with the draw-off cap provided and tighten firmly.
- Thread the draw-off tubing through the anti-kink spring. Attach the tube to the draw-off cap. Screw the spring clockwise over the tubing and draw-off spigot.
- Invert the backpack.
- Set the dose at the maximum (50 mL) by unscrewing the adjuster at the base of the handle. Gently prime the applicator, checking for leaks. To prime, point the nozzle into a clean, dry receptacle and gently pump the lever back and forth to expel air from the system. When the barrel completely fills after every priming stroke, set the dose.
- Set the dose as follows:
  - a)Use the handle to align the middle of the blue plunger ring with the chosen mark on the barrel. Tighten the adjuster screw against the handle.
  - b)Secure the dose with the adjuster screw locknut.
  Note: Dose accuracy can be checked by dispensing a known number of set doses into a measuring cylinder. Correct any inaccuracy by adjusting the dose setting screw. Repeat this procedure until desired accuracy is achieved.
- Administer each dose by fully depressing the handle so that the plunger travels its entire set length. Release the handle and the applicator will automatically refill.
- To disconnect the system proceed as follows:
  - a)Set backpack in upward position.
  - b)Discharge residual material from the applicator and draw off tubing into a separate, dry receptacle.
- Follow the manufacturer's recommendation for care and maintenance of the dosing applicator.
- Remove the draw-off cap. Replace with the original cap and tighten firmly.

WARNING

Flammable! Keep away from heat, sparks, open flame, and other sources of ignition. Not for human use. Keep out of reach of children. The Safety Data Sheet (SDS) contains more detailed occupational safety information. To report adverse effects in users, to obtain more information, or to obtain an SDS, call 1-888-963-8471.
Dectomax Pour-On solution for cattle may be irritating to human skin and eyes, and users should be careful not to apply it to themselves or to other persons. Operators should wear protective clothing including a long-sleeved shirt, protective gloves, and boots with a waterproof coat when applying the product. Protective clothing should be washed after use. If accidental skin contact occurs, wash the affected area immediately with soap and water. If accidental eye exposure occurs, flush the eyes immediately with water and get medical attention.

OTHER WARNINGS

Parasite resistance may develop to any dewormer, and has been reported for most classes of dewormers. Treatment with a dewormer used in conjunction with parasite management practices appropriate to the geographic area and the animal(s) to be treated may slow the development of parasite resistance. Fecal examinations or other diagnostic tests and parasite management history should be used to determine if the product is appropriate for the herd prior to the use of any dewormer. Following the use of any dewormer, effectiveness of treatment should be monitored (for example, with the use of a fecal egg count reduction test or another appropriate method). A decrease in a drug’s effectiveness over time as calculated by fecal egg count reduction tests may indicate the development of resistance to the dewormer administered. Your parasite management plan should be adjusted accordingly based on regular monitoring.

RESIDUE WARNING

Cattle must not be slaughtered for human consumption within 45 days of treatment. Not for use in female dairy cattle 20 months of age or older. A withdrawal period has not been established for this product in preruminating calves. Do not use in calves to be processed for veal.

PRECAUTIONS

Dectomax Pour-On solution has been developed specifically for use in cattle only. This product should not be used in other animal species as severe adverse reactions, including fatalities in dogs, may result.

This product is to be applied to skin surface only. Do not administer orally or parenterally.

Do not apply to areas of skin which are caked with mud or manure.

Wash hands after use.

Do not smoke or eat while handling the product.

Cloudiness in the formulation may occur when Dectomax Pour-On solution is stored at temperatures below 0°C (32°F). Allowing to warm to room temperature will restore the normal appearance without affecting efficacy.

Dectomax Pour-On solution is highly effective against cattle grubs. However, proper timing of treatment is important. For most effective results, cattle should be treated as soon as possible after the end of the heel fly (warble) season.

Destruction of Hypoderma larvae (cattle grubs) at the period when these grubs are in vital areas may cause undesirable host-parasite reactions including the possibility of fatalities. Killing H. lineatum when it is in the tissue surrounding the gullet may cause bloat; killing H. bovis when it is in the vertebral canal may cause staggering or paralysis. These reactions are not specific to treatment with Dectomax Pour-On solution, but can occur with any successful treatment of grubs. Cattle should be treated either before or after the migratory phase of grub development. Consult your veterinarian concerning the proper time for treatment.

Cattle treated with Dectomax Pour-On solution after the end of heel fly season may be re-treated with Dectomax Pour-On during the winter for internal parasites, mange mites, or biting and sucking lice, without danger of grub-related reactions. A planned parasite control program is recommended.

USE CONDITIONS

Varying weather conditions, including rainfall, do not affect the efficacy of Dectomax Pour-On.

ENVIRONMENTAL SAFETY

Studies indicate that when doramectin comes in contact with the soil, it readily and tightly binds to the soil and becomes inactive over time. Free doramectin may adversely affect fish and certain aquatic organisms. Do not permit cattle to enter lakes, streams or ponds for at least 6 hours after treatment. Do not contaminate water by direct application or by the improper disposal of drug containers. Dispose of containers in an approved landfill or by incineration. As with other avermectins, doramectin is excreted in the dung of treated animals and can inhibit the reproduction and growth of pest and beneficial insects that use dung as a source of food and for reproduction. The magnitude and duration of such effects are species and life-cycle specific. When used according to label directions, the product is not expected to have an adverse impact on populations of dung-dependent insects.

STORAGE AND HANDLING

Store Below 30°C (86°F)

Protect From Light

HOW SUPPLIED

Dectomax Pour-On solution is available in 1-L (0.26 gal), 2.5-L (0.66 gal), 5-L (1.32 gal) multi-dose containers.

Approved by FDA under NADA # 141-095
Consult your veterinarian for assistance in the diagnosis, treatment, and control of parasitism.
Not for human use.
Restricted Drug (CA) Use only as directed.
zoetis
Manufactured and Distributed by:
Zoetis Inc.
Kalamazoo, MI 49007

Revised: May 2023
40043635

PRINCIPAL DISPLAY PANEL - 1 L Bottle Carton

40043639

PRINCIPAL DISPLAY PANEL - 2.5 L Jug Carton

40043653

PRINCIPAL DISPLAY PANEL - 5 L Jug Carton

40043657